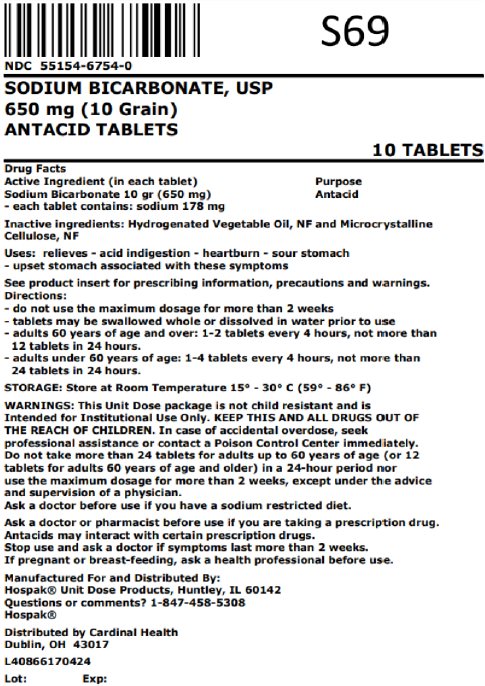 DRUG LABEL: Sodium Bicarbonate
NDC: 55154-6754 | Form: TABLET
Manufacturer: Cardinal Health 107, LLC
Category: otc | Type: HUMAN OTC DRUG LABEL
Date: 20241107

ACTIVE INGREDIENTS: SODIUM BICARBONATE 650 mg/1 1
INACTIVE INGREDIENTS: MINERAL OIL; STARCH, CORN

Sodium Bicarbonate 650 mg (10 grain)

Active ingredient

Drug Facts

In each tablet: Sodium Bicarbonate 10 gr (650 mg)

- Each tablet contains: sodium 178 mg

Purpose

Antacid

Indications and Usage

Relieves -

- acid indigestion
- heartburn
- sour stomach
- upset stomach associated with these symptoms

Keep Out of Reach of Children

KEEP THIS AND ALL DRUGS OUT OF THE REACH OF CHILDREN.. In case of accidental overdose, seek professional assistance or contact a Poison Control Center immediately.

Warnings

This Unit Dose package is not child resistant and is Intended for Institutional Use Only.

Do not take more than 24 tablets for adults up to 60 years of age (or 12 tablets for adults 60 years of age and older) in a 24-hour period nor use the maximum dosage for more than 2 weeks, except under the advice and supervision of a physician.

Ask a doctor before use if you have a sodium restricted diet.

Ask a doctor or pharmacist before use if you are taking a prescription drug. Antacids may interact with certain prescription drugs.

Stop use and ask a doctor if symptoms last more than 2 weeks.

If you are pregnant or breast-feeding, ask a health professional before use.

Directions

See product insert for prescribing information, precautions and warnings.

- Do not use the maximum dosage for more than 2 weeks
- Tablets may be swallowed whole or dissolved in water prior to use
- Adults 60 years of age or over: 1-2 every 4 hours, not more than 12 tablets in 24 hours.
- Adults under 60 years of age: 1-4 tablets every 4 hours, not more than 24 tablets in 24 hours.

Inactive ingredients

Hydrogenated Vegetable Oil, NF and Microcrystalline Cellulose, NF

Storage and Handling

Store at room temperature 15° - 30°C (59° - 86°F)

Other

Manufactured For and Distributed By:

Hospak® Unit Dose Products, Huntley, IL 60142

Questions or comments? 1-847-458-5308

Hospak®

Distributed By:

Cardinal Health

Dublin, OH 43017

L40866170518

Rev. 8/17

Principal Display Panel

SODIUM BICARBONATE, USP

650 mg (10 Grain)

ANTACID TABLETS

10 TABLETS